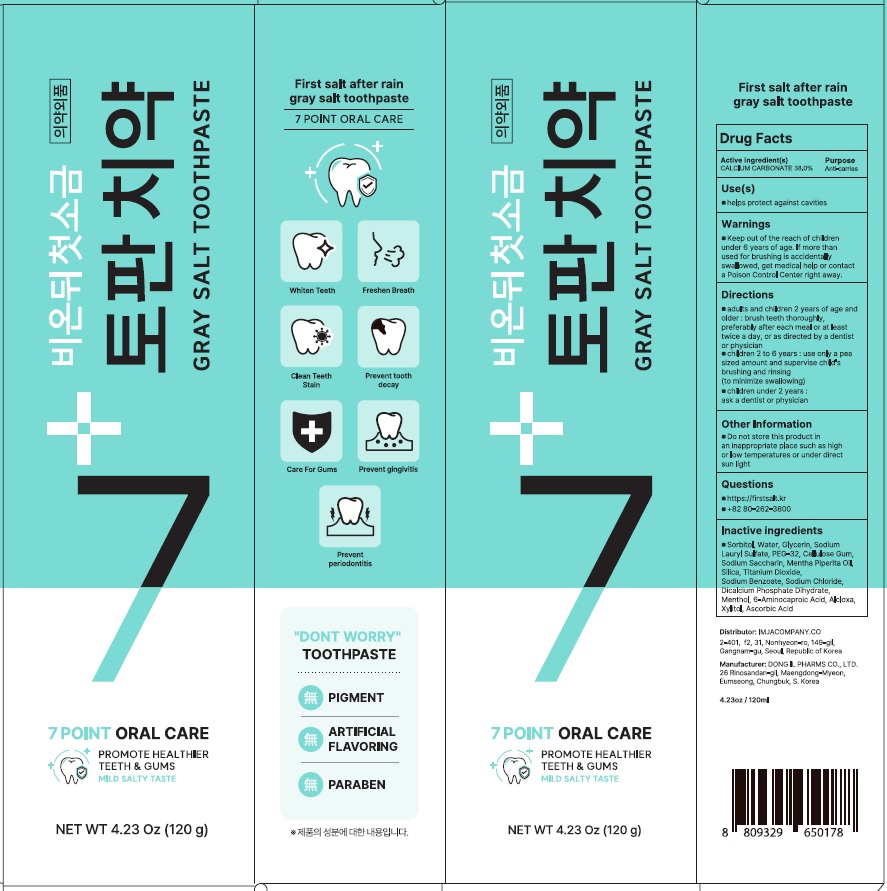 DRUG LABEL: First salt after rain gray salt toothpaste
NDC: 83876-010 | Form: PASTE, DENTIFRICE
Manufacturer: IMJACOMPANY.CO
Category: otc | Type: HUMAN OTC DRUG LABEL
Date: 20240111

ACTIVE INGREDIENTS: CALCIUM CARBONATE 38.0 g/100 g
INACTIVE INGREDIENTS: Sorbitol; Water

ACTIVE INGREDIENT

CALCIUM CARBONATE 38.0%

Inactive ingredients

Sorbitol, Water, Glycerin, Sodium Lauryl Sulfate, PEG-32, Cellulose Gum, Sodium Saccharin, Mentha Piperita Oil, Silica, Titanium Dioxide, Sodium Benzoate, Sodium Chloride, Dicalcium Phosphate Dihydrate, Menthol, 6-Aminocaproic Acid, Alcloxa, Xylitol, Ascorbic Acid

PURPOSE

Anti-carries

WARNINGS

Keep out of the reach of children under 6 years of age.

If more than used for brushing is accidentally swallowed, get medical help or contact a Poison Control Center right away.

KEEP OUT OF REACH OF CHILDREN

Keep out of the reach of children under 6 years of age.

Uses

helps protect against cavities.

Directions

■ adults and children 2 years of age and older : brush teeth thoroughly, preferably after each meal or at least twice a day, or as directed by a dentist or physician
■ children 2 to 6 years : use only a pea sized amount and supervise child's brushing and rinsing (to minimize swallowing)
■ children under 2 years : ask a dentist or physician

Other Information

Do not store this product in an inappropriate place such as high or low temperatures or under direct sun light.

Questions

https://firstsalt.kr
+82 80-262-3800